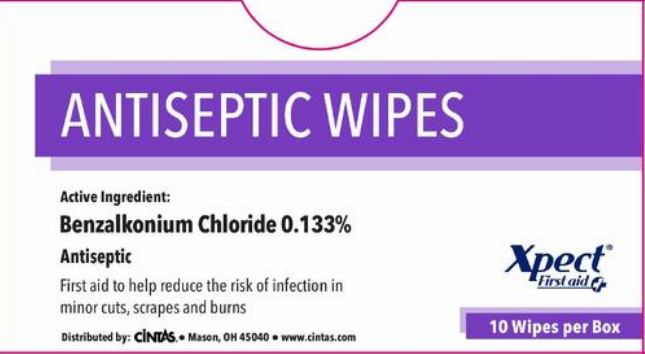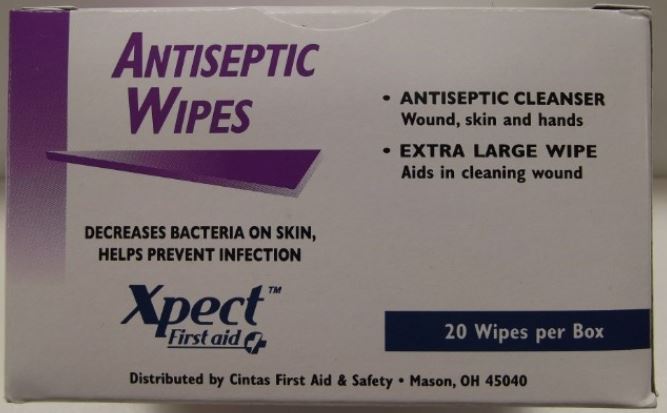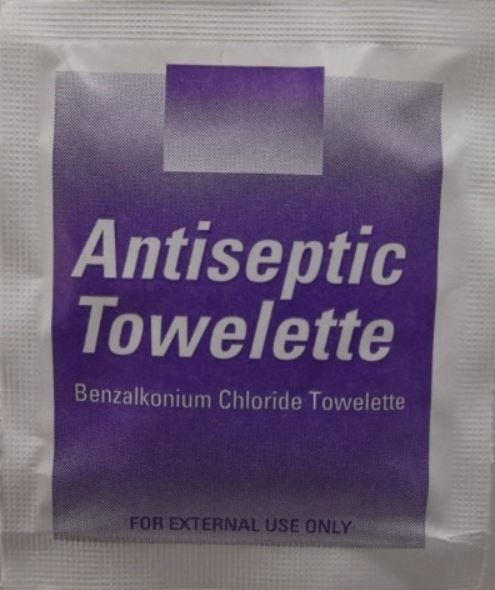 DRUG LABEL: Xpect Antiseptic Wipes
NDC: 42961-022 | Form: SPONGE
Manufacturer: Cintas Corporation
Category: otc | Type: HUMAN OTC DRUG LABEL
Date: 20250929

ACTIVE INGREDIENTS: BENZALKONIUM CHLORIDE .13 mg/.13 mg
INACTIVE INGREDIENTS: WATER; SODIUM BICARBONATE

Xpect Antiseptic Wipes

Active Ingredients

Benzalkonium Chloride 0.133%

Purpose

Antiseptic

Uses

First aid to reduce bacteria in minor cuts, scrapes and burns

Warnings

For external use only

Do not use in the eyes or apply over large areas of the body

Ask a doctor before use if you have deep or puncture wounds or serious burns

Stop use and ask a doctor if condition persists or gets worse

Keep out of reach of children. If swallowed, get medical help or contact a Poison Control Center right away

Directions

Clean the affected area

Other Information

- do not use if packet is torn, cut or opened
- store at room temperature

Inactive ingredients

sodium bicarbonate, water

Questions or comments? Call 1-877-973-2811 Monday-Friday 8 am - 5 pm

Principal Display Panel - 20 Count Box

ANTISEPTIC WIPES

DECREASES BACTERIA ON SKIN, HELPS PREVENT INFECTION

Xpect™ First Aid

- ANTISEPTIC CLEANSER

Wound, skin and hands

- EXTRA LARGE WIPE

Aids in cleaning wound

20 Wipes per Box

Distributed by Cintas First Aid & Safety • Mason, OH 45040

Principal Display Panel - Packet

Antiseptic Towelette

Benzalkonium Chloride Towelette

FOR EXTERNAL USE ONLY

Principal Display Panel - 10 Count Box

ANTISEPTIC WIPES

Active Ingredient:

Benzalkonium Chloride 0.133%

Antiseptic

First aid to help reduce the risk of infection in minor cuts, scrapes and burns

Distributed by: Cintas® • Mason, OH 45040 • www.cintas.com

Xpect® First Aid

10 Wipes per Box